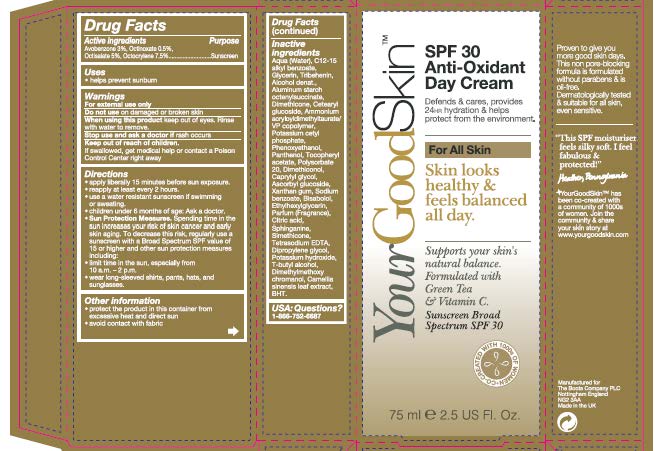 DRUG LABEL: YourGoodSkin SPF 30 Anti-oxidant Day Sunscreen Broad Spectrum SPF 30
NDC: 11489-112 | Form: CREAM
Manufacturer: BCM Ltd
Category: otc | Type: HUMAN OTC DRUG LABEL
Date: 20171101

ACTIVE INGREDIENTS: AVOBENZONE 2.25 g/75 g; OCTINOXATE 0.375 g/75 g; OCTISALATE 3.75 g/75 g; OCTOCRYLENE 5.625 g/75 g
INACTIVE INGREDIENTS: WATER; ALKYL (C12-15) BENZOATE; GLYCERIN; TRIBEHENIN; ALCOHOL; DIMETHICONE; ALUMINUM STARCH OCTENYLSUCCINATE; CETEARYL GLUCOSIDE; AMMONIUM ACRYLOYLDIMETHYLTAURATE/VP COPOLYMER; POTASSIUM CETYL PHOSPHATE; PHENOXYETHANOL; PANTHENOL; .ALPHA.-TOCOPHEROL ACETATE; POLYSORBATE 20; DIMETHICONOL (2000 CST); CAPRYLYL GLYCOL; ASCORBYL GLUCOSIDE; XANTHAN GUM; SODIUM BENZOATE; .ALPHA.-BISABOLOL, (+)-; ETHYLHEXYLGLYCERIN; CITRIC ACID MONOHYDRATE; SPHINGANINE; EDETATE SODIUM TETRAHYDRATE; DIPROPYLENE GLYCOL; POTASSIUM HYDROXIDE; TERT-BUTYL ALCOHOL; DIMETHYLMETHOXY CHROMANOL; SILICON DIOXIDE; GREEN TEA LEAF; BUTYLATED HYDROXYTOLUENE

YourGoodSkinTM SPF 30 Anti-oxidant Day (Sunscreen Broad Spectrum SPF 30)

Carton

Active ingredients

Avobenzone 3%

Octinoxate 0.5%

Octisalate 5%

Octocrylene 7.5%

Purpose

Sunscreen

Uses

- Uses helps prevent sunburn

Warnings

For external use only

Do not use on damaged or broken skin

When using this product keep out of eyes. Rinse with water to remove.

Ask Doctor section

Stop use and ask a doctor if rash occurs

Keep out of reach of children.

If swallowed, get medical help or contact a Poison Control Centre right away

Directions

- Apply liberally 15 minutes before sun exposure
- reapply at least every 2 hours
- use a water resistant sunscreen if swimming or sweating
- children under 6 months of age: Ask a doctor
- Sun Protection Measures. Spending time in the sun increases your risk of skin cancer and early skin aging. To decrease this risk, regularly use a sunscreen with a Broad Spectrum SPF value of 15 or higher and other sun protection measures including:
- Limit time in the sun, especially from 10 a.m - 2 p.m.
- wear long-sleeved shirts,pants,hats and sunglasses.

Other information

- protect the product in this container from excessive heat and direct sun
- avoid contact with fabric

Inactive ingredients

Inactive ingredients Aqua (Water), C12-15 alkyl benzoate, Glycerin, Tribehenin, Alcohol denat., Dimethicone, Aluminum starch octenylsuccinate, Cetearyl glucoside, Ammonium acryloldimethyltaurate/VP copolymer, Potassium cetyl phosphate, Phenoxyethanol, Panthenol, Tocopheryl acetate, Polysorbate 20, Dimethiconol, Caprylyl glycol, Ascorbyl glucoside, Xanthan gum, Sodium benzoate, Bisabolol, Ethylhexylglycerin, Parfum (Fragrance), Citric acid, Sphinganine, Tetrasodium EDTA, Dipropylene glycol, Potassium hydroxide, T-butyl alcohol, Dimethylmethoxy chromanol, Silica, Camellia sinensis leaf extract, BHT.

Questions

USA: Questions? 1-866-752-6687

Information

Manufactured for The Boots Company PLC Nottingham England NG2 3AA

Made in the UK

Description

Defends & cares, provides 24hr hydration & helps protect from the environment.

For All Skin

Skin looks healthy & feels balanced all day.

Supports your skin's natural balance.

Formulated with Green Tea & Vitamin C.

Sunscreen Broad Spectrum SPF 30

Proven to give you more good skin days. This non pore-blocking formula is formulated without parabens & is oil-free. Dermatologically tested & suitable for all skin, even sensitive.

YourGoodSkinTM has been co-created with a community of 1000s of women. Join the community & share your skin story at www.yourgoodskin.com.

Tube wording

YourGoodSkinTM SPF 30 Anti-Oxidant Day Cream

Defends & cares, provides 24hr hydration & helps protect from the environment.

For All Skin

Skin looks healty & feels balanced all day.

Supports your skin's natural balance.

Formulated with Green Tea & Vitamin C.

Sunscreen Broad Spectrum SPF 30

YourGoodSkinTM Guide

Dot across your cheeks, chin & forehead & gently blend together ensuring all skin is covered. Use each morning after your Balancing Skin Concentrate.

Make sure it does not get into your eyes. If it does then rinse well with water immediately. Avoid contact with fabric.

Proven to give you more good skin days. This non-pore blocking formula is formulated without parabens & is oil-free. Dermatologically tested & suitable for all skin, even sensitive.

Active Ingredients: Avobenzone 3% Octinoxate 0.5% Octisalate 5% Octocrylene 7.5%

Manufactured for The Boots Company PLC Nottingham England NG2 3AA

Made in the UK

www.yourgoodskin.com

Carton